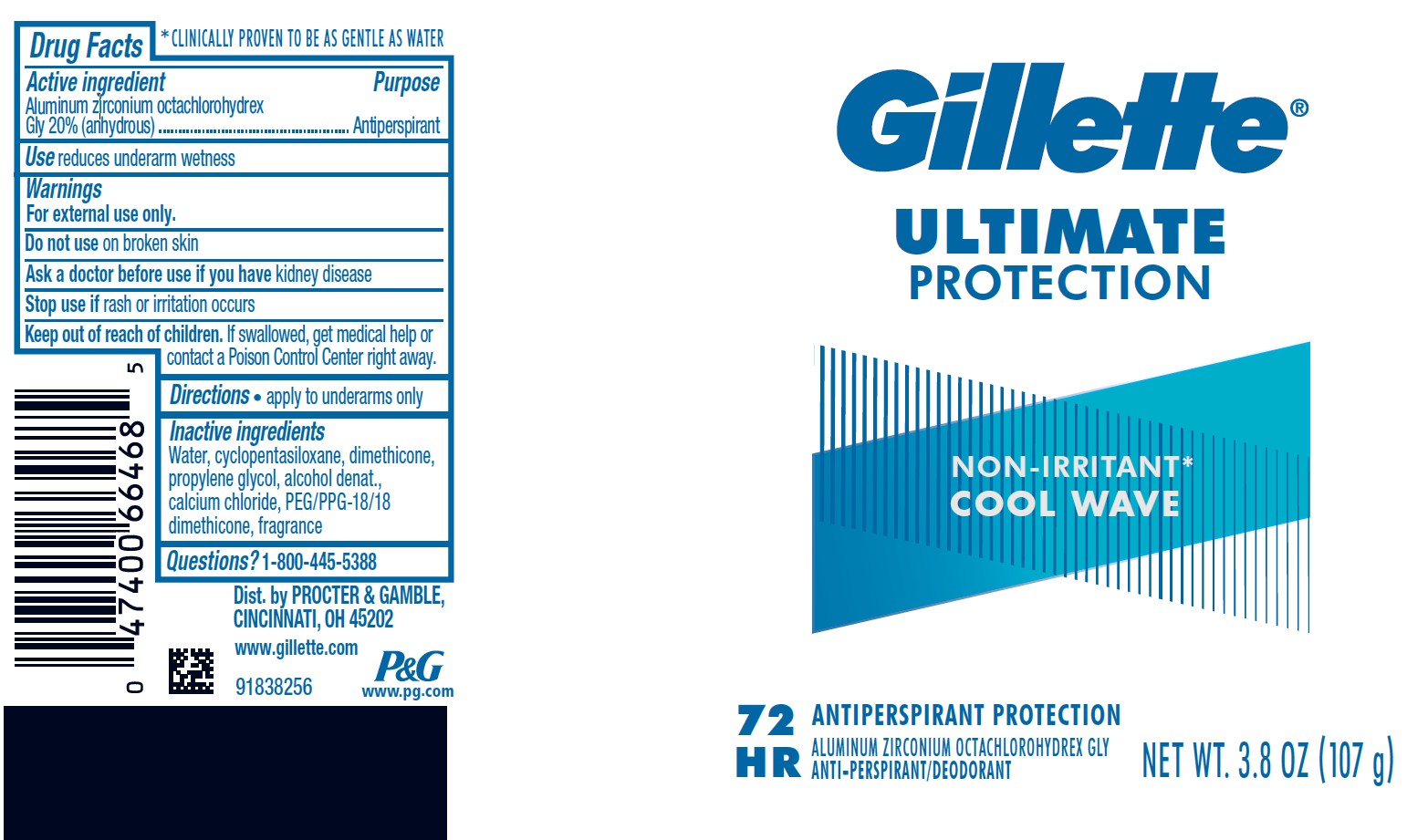 DRUG LABEL: Gillette Ultimate Protection Cool Wave
NDC: 84126-224 | Form: GEL
Manufacturer: The Procter & Gamble Manufacturing Company
Category: otc | Type: HUMAN OTC DRUG LABEL
Date: 20260225

ACTIVE INGREDIENTS: ALUMINUM ZIRCONIUM OCTACHLOROHYDREX GLY 20 g/100 g
INACTIVE INGREDIENTS: CYCLOPENTASILOXANE; WATER; DIMETHICONE; PROPYLENE GLYCOL; CALCIUM CHLORIDE; PEG/PPG-18/18 DIMETHICONE; ALCOHOL

Drug Facts

Active ingredient

Aluminum zirconium octachlorohydrex Gly 20% (anhydrous)

Purpose

Antiperspirant

Use

reduces underarm wetness

Warnings

For external use only.

Do not use on broken skin

Ask a doctor before use if you have kidney disease

Stop use if rash or irritation occurs

Keep out of reach of children. If swallowed, get medical help or contact a Poison Control Center right away.

Directions

- apply to underarms only

Inactive ingredients

water, cyclopentasiloxane, dimethicone, propylene glycol, alcohol denat., calcium chloride, PEG/PPG-18/18 dimethicone, fragrance

Questions?

1-800-445-5388

Dist. by PROCTER & GAMBLE,
CINCINNATI, OH 45202.

PACKAGE LABEL

Gillette

ULTIMATE

PROTECTION

NON-IRRITANT

COOL WAVE
72 HR

ANTIPERSPIRANT PROTECTION

ALUMINUM ZIRCONIUM OCTACHLOROHYDREX GLY

ANTI-PERSPIRANT/DEODORANT

NET WT. 3.8 OZ (107 g)